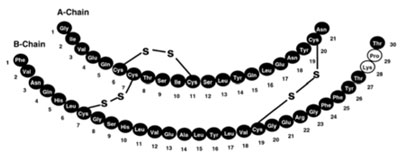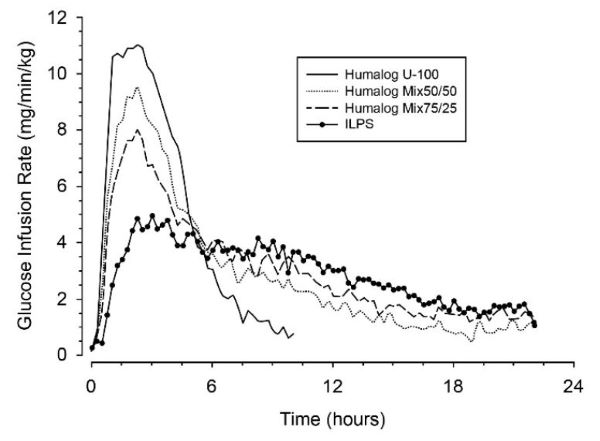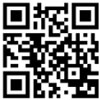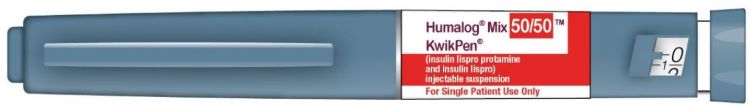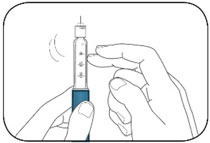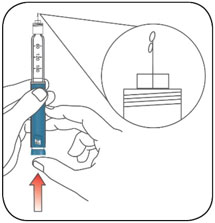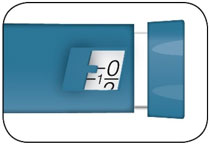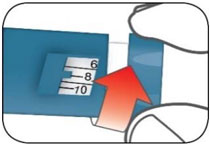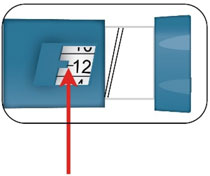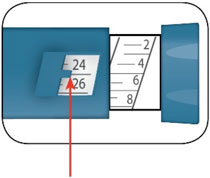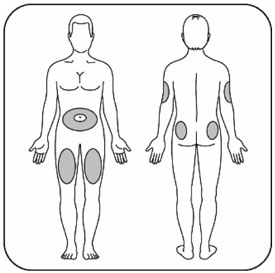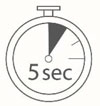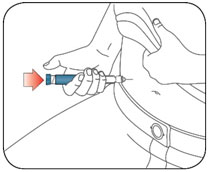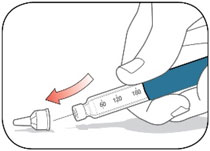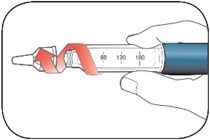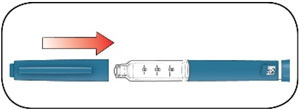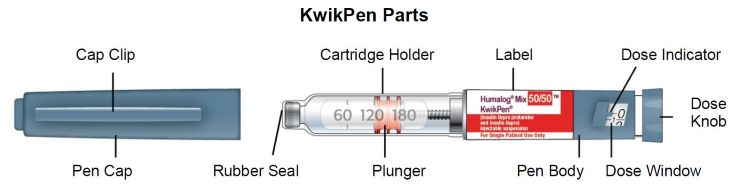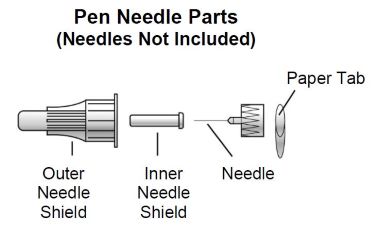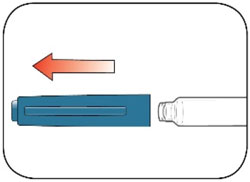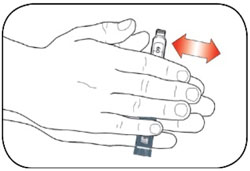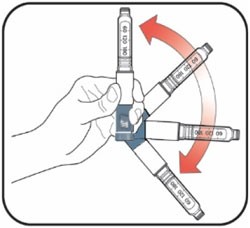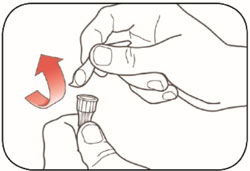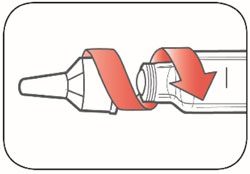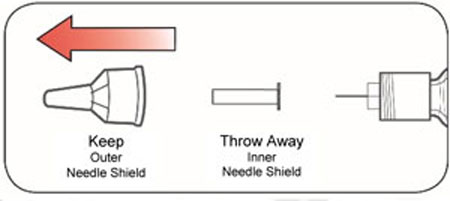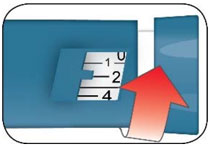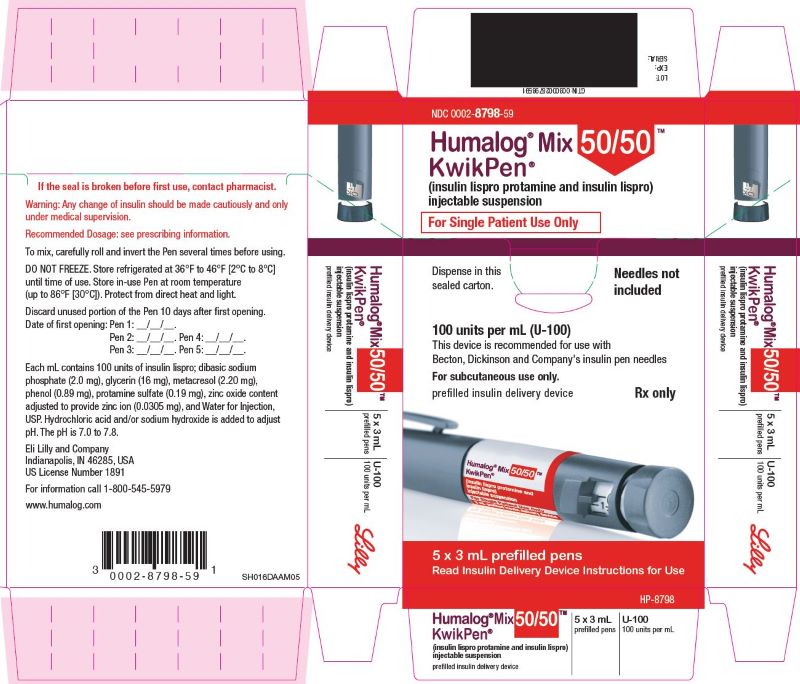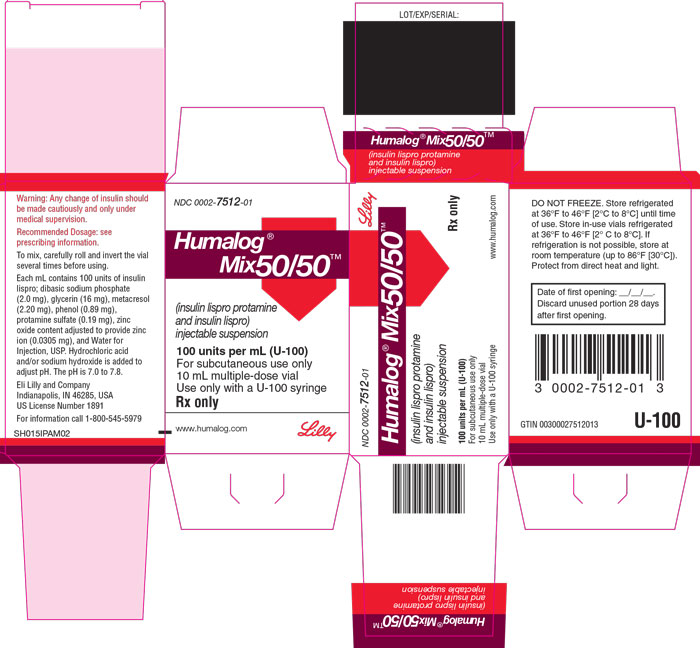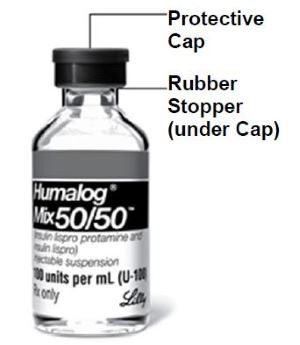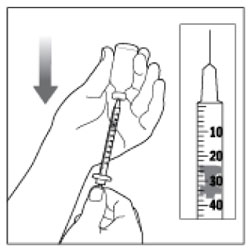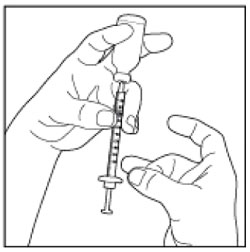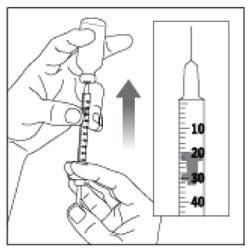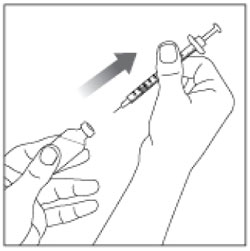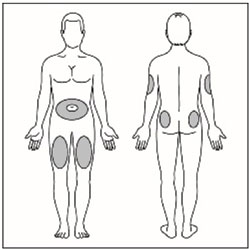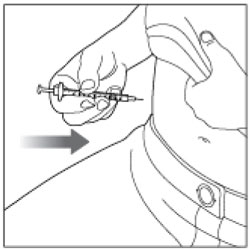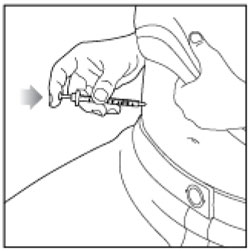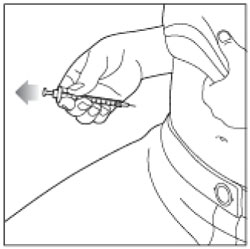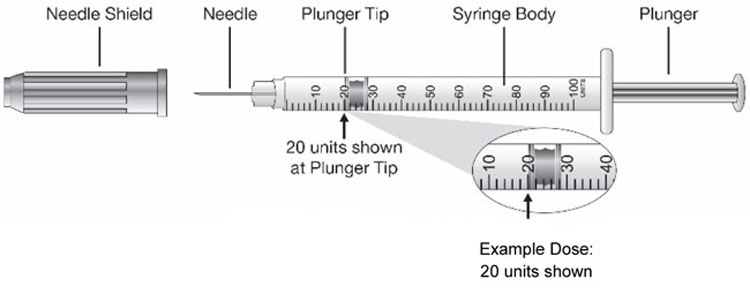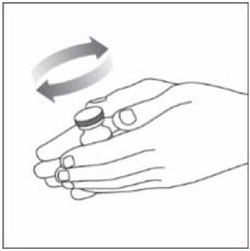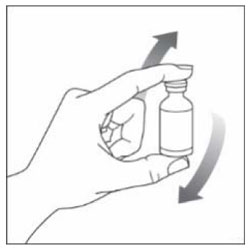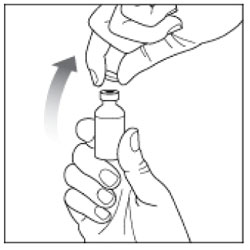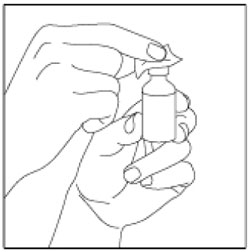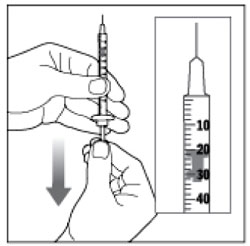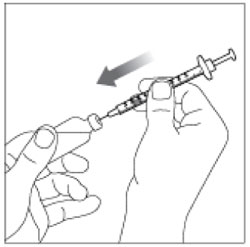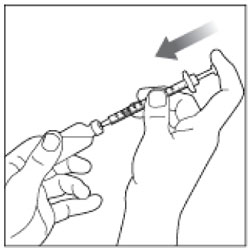 DRUG LABEL: Humalog 
NDC: 0002-7512 | Form: INJECTION, SUSPENSION
Manufacturer: Eli Lilly and Company
Category: prescription | Type: HUMAN PRESCRIPTION DRUG LABEL
Date: 20241113

ACTIVE INGREDIENTS: Insulin lispro 100 [iU]/1 mL
INACTIVE INGREDIENTS: Protamine sulfate 0.19 mg/1 mL; Glycerin 16 mg/1 mL; Sodium Phosphate, Dibasic, Unspecified Form 3.78 mg/1 mL; Metacresol 2.2 mg/1 mL; Zinc oxide .0305 mg/1 mL; Phenol .89 mg/1 mL; Water; Hydrochloric acid; Sodium hydroxide

HIGHLIGHTS OF PRESCRIBING INFORMATION

These highlights do not include all the information needed to use HUMALOG MIX50/50 safely and effectively. See full prescribing information for HUMALOG MIX50/50.
HUMALOG MIX50/50 (insulin lispro protamine and insulin lispro) injectable suspension, for subcutaneous use
Initial U.S. Approval: 1999

1 INDICATIONS AND USAGE

HUMALOG® Mix50/50™ is a mixture of insulin lispro protamine, an intermediate-acting human insulin analog, and insulin lispro, a rapid-acting human insulin analog, indicated to improve glycemic control in adults with diabetes mellitus. (1)

Limitations of Use:

The proportions of rapid-acting and intermediate-acting insulins are fixed and do not allow for basal versus prandial dose adjustments. (1)

2 DOSAGE AND ADMINISTRATION

- See Full Prescribing Information for important preparation and administration instructions. (2.1)
- Inject HUMALOG Mix50/50 subcutaneously (within 15 minutes before a meal) in abdominal wall, thigh, upper arm, or buttocks and rotate injection sites to reduce the risk of lipodystrophy and localized cutaneous amyloidosis. (2.1, 2.2)
- Individualize and adjust dosage based on metabolic needs, blood glucose monitoring results and glycemic control goal. (2.2)
- Do not administer HUMALOG Mix50/50 intravenously or by a continuous subcutaneous insulin infusion pump. (2.1)
- HUMALOG Mix50/50 is typically dosed twice daily (with each dose intended to cover 2 meals or a meal and a snack). (2.2)

3 DOSAGE FORMS AND STRENGTHS

Injectable suspension: 100 units/mL (U-100) of HUMALOG Mix50/50, 50% insulin lispro protamine and 50% insulin lispro available as: (3)

- 10 mL multiple-dose vial
- 3 mL single-patient-use KwikPen® prefilled pen

4 CONTRAINDICATIONS

- Do not use during episodes of hypoglycemia. (4)
- Do not use in patients with hypersensitivity to HUMALOG Mix50/50 or any of its excipients. (4)

5 WARNINGS AND PRECAUTIONS

- Never share a HUMALOG Mix50/50 KwikPen or syringe between patients, even if the needle is changed. (5.1)
- Hyperglycemia or Hypoglycemia with Changes in Insulin Regimen: Make changes to a patient's insulin regimen (e.g., insulin strength, manufacturer, type, injection site or method of administration) under close medical supervision with increased frequency of blood glucose monitoring. (5.2)
- Hypoglycemia: May be life-threatening. Increase frequency of blood glucose monitoring with changes to insulin dosage, co-administered glucose lowering medications, meal pattern, physical activity; in patients with renal or hepatic impairment; and in patients with hypoglycemia unawareness. (5.3)
- Hypoglycemia Due to Medication Errors: Accidental mix-ups between insulin products can occur. Instruct patients to check insulin labels before injection. (5.4)
- Hypersensitivity Reactions: Severe, life-threatening, generalized allergy, including anaphylaxis, can occur. Discontinue HUMALOG Mix50/50, monitor and treat if indicated. (5.5)
- Hypokalemia: May be life-threatening. Monitor potassium levels in patients at risk of hypokalemia and treat if indicated. (5.6)
- Fluid Retention and Heart Failure with Concomitant Use of Thiazolidinediones (TZDs): Observe for signs and symptoms of heart failure; consider dosage reductions or discontinuation if heart failure occurs. (5.7)

6 ADVERSE REACTIONS

Adverse reactions observed with HUMALOG Mix50/50 include hypoglycemia, allergic reactions, injection site reactions, lipodystrophy, weight gain, edema, pruritus, and rash. (6)

To report SUSPECTED ADVERSE REACTIONS, contact Eli Lilly and Company at 1-800-LillyRx (1-800-545-5979) or FDA at 1-800-FDA-1088 or www.fda.gov/medwatch.

7 DRUG INTERACTIONS

- Drugs that may increase the risk of hypoglycemia: antidiabetic agents, ACE inhibitors, angiotensin II receptor blocking agents, disopyramide, fibrates, fluoxetine, monoamine oxidase inhibitors, pentoxifylline, pramlintide, salicylates, somatostatin analog (e.g., octreotide), and sulfonamide antibiotics. (7)
- Drugs that may decrease the blood glucose lowering effect: atypical antipsychotics, corticosteroids, danazol, diuretics, estrogens, glucagon, isoniazid, niacin, oral contraceptives, phenothiazines, progestogens (e.g., in oral contraceptives), protease inhibitors, somatropin, sympathomimetic agents (e.g., albuterol, epinephrine, terbutaline), and thyroid hormones. (7)
- Drugs that may increase or decrease the blood glucose lowering effect: alcohol, beta-blockers, clonidine, lithium salts, and pentamidine. (7)
- Drugs that may blunt the signs and symptoms of hypoglycemia: beta-blockers, clonidine, guanethidine, and reserpine. (7)

FULL PRESCRIBING INFORMATION

1 INDICATIONS AND USAGE

HUMALOG Mix50/50 is indicated to improve glycemic control in adults with diabetes mellitus.

Limitations of Use

The proportions of rapid-acting and intermediate-acting insulins in HUMALOG Mix50/50 are fixed and do not allow for basal versus prandial dose adjustments.

2 DOSAGE AND ADMINISTRATION

2.1 Important Preparation and Administration Instructions

Preparation Instructions

- Always check insulin labels before administration [see Warnings and Precautions (5.4)].
- HUMALOG Mix50/50 is a suspension that must be resuspended immediately before use. Resuspension is easier when the insulin has reached room temperature.
- To resuspend the
  - vial, carefully invert the vial at least 10 times until the suspension appears uniformly white and cloudy.
  - KwikPen, gently roll the KwikPen at least 10 times and then carefully invert the KwikPen at least 10 times until the suspension appears uniformly white and cloudy.
- Inspect HUMALOG Mix50/50 visually before use. Do not use if discoloration or particulate matter is seen.

Administration Instructions

- After resuspension, immediately administer HUMALOG Mix50/50 by subcutaneous injection into the abdominal wall, thigh, upper arm, or buttocks.
- Rotate the injection site within the same region from one injection to the next to reduce the risk of lipodystrophy and localized cutaneous amyloidosis. Do not inject into areas of lipodystrophy or localized cutaneous amyloidosis [see Warnings and Precautions (5.2) and Adverse Reactions (6)].
- The HUMALOG Mix50/50 KwikPen dials in 1 unit increments.
- Use HUMALOG Mix50/50 KwikPen with caution in patients with visual impairment that may rely on audible clicks to dial their dose.
- Do not administer HUMALOG Mix50/50 intravenously or by a continuous subcutaneous insulin infusion pump.
- Do not mix HUMALOG Mix50/50 with any other insulins or diluents.

2.2 Dosage Recommendations

- Individualize and adjust the dosage of HUMALOG Mix50/50 based on the individual's metabolic needs, blood glucose monitoring results and glycemic control goal.
- Inject HUMALOG Mix50/50 subcutaneously within 15 minutes before a meal.
- HUMALOG Mix50/50 is typically dosed twice-daily (with each dose intended to cover 2 meals or a meal and a snack).
- Dosage adjustments may be needed with changes in physical activity, changes in meal patterns (i.e., macronutrient content or timing of food intake), changes in renal or hepatic function or during acute illness [see Warnings and Precautions (5.2, 5.3) and Use in Specific Populations (8.6, 8.7)].
- When switching from another insulin to HUMALOG Mix50/50, a different dosage of HUMALOG Mix50/50 may be needed.
- During changes to a patient's insulin regimen, increase the frequency of blood glucose monitoring [see Warnings and Precautions (5.2)].

2.3 Dosage Modifications for Drug Interactions

Dosage modification may be needed when HUMALOG Mix50/50 is used concomitantly with certain drugs [see Drug Interactions (7)].

3 DOSAGE FORMS AND STRENGTHS

Injectable suspension: 100 units/mL (U-100) of HUMALOG Mix50/50, 50% insulin lispro protamine and 50% insulin lispro, is a white and cloudy suspension available as:

- 10 mL multiple-dose vial
- 3 mL single-patient-use KwikPen prefilled pen

4 CONTRAINDICATIONS

HUMALOG Mix50/50 is contraindicated:

- during episodes of hypoglycemia [see Warnings and Precautions (5.3)]
- in patients who have had hypersensitivity reactions to HUMALOG Mix50/50 or to any of its excipients [see Warnings and Precautions (5.5)]

5 WARNINGS AND PRECAUTIONS

5.1 Never Share a HUMALOG Mix50/50 KwikPen or Syringe Between Patients

HUMALOG Mix50/50 KwikPens must never be shared between patients, even if the needle is changed. Patients using HUMALOG Mix50/50 vials must never share needles or syringes with another person. Sharing poses a risk for transmission of blood-borne pathogens.

5.2 Hyperglycemia or Hypoglycemia with Changes in Insulin Regimen

Changes in an insulin regimen (e.g., insulin strength, manufacturer, type, injection site or method of administration) may affect glycemic control and predispose to hypoglycemia [see Warnings and Precautions (5.3)] or hyperglycemia. Repeated insulin injections into areas of lipodystrophy or localized cutaneous amyloidosis have been reported to result in hyperglycemia; and a sudden change in the injection site (to an unaffected area) has been reported to result in hypoglycemia [see Adverse Reactions (6)].

Make any changes to a patient's insulin regimen under close medical supervision with increased frequency of blood glucose monitoring. Advise patients who have repeatedly injected into areas of lipodystrophy or localized cutaneous amyloidosis to change the injection site to unaffected areas and closely monitor for hypoglycemia. For patients with type 2 diabetes, dosage adjustments of concomitant anti-diabetic products may be needed.

5.3 Hypoglycemia

Hypoglycemia is the most common adverse reaction associated with all insulins, including HUMALOG Mix50/50. Severe hypoglycemia can cause seizures, may lead to unconsciousness, may be life-threatening, or cause death. Hypoglycemia can impair concentration ability and reaction time, this may place an individual and others at risk in situations where these abilities are important (e.g., driving or operating other machinery).

Hypoglycemia can happen suddenly, and symptoms may differ in each individual and change over time in the same individual. Symptomatic awareness of hypoglycemia may be less pronounced in patients with longstanding diabetes, in patients with diabetic nerve disease, in patients using medications that block the sympathetic nervous system (e.g., beta-blockers) [see Drug Interactions (7)], or in patients who experience recurrent hypoglycemia.

Risk Factors for Hypoglycemia

The risk of hypoglycemia after an injection is related to the duration of action of the insulin and in general, is highest when the glucose lowering effect of the insulin is maximal. As with all insulins, the glucose lowering effect time course of HUMALOG Mix50/50 may vary in different individuals or at different times in the same individual and depends on many conditions, including the area of injection as well as the injection site blood supply and temperature [see Clinical Pharmacology (12.2)]. Other factors which may increase the risk of hypoglycemia include changes in meal pattern (e.g., macronutrient content or timing of meals), changes in level of physical activity, or changes to co-administered medication [see Drug Interactions (7)]. Patients with renal or hepatic impairment may be at higher risk of hypoglycemia [see Use in Specific Populations (8.6, 8.7)].

Risk Mitigation Strategies for Hypoglycemia

Patients and caregivers must be educated to recognize and manage hypoglycemia. Self-monitoring of blood glucose plays an essential role in the prevention and management of hypoglycemia. In patients at higher risk for hypoglycemia and patients who have reduced symptomatic awareness of hypoglycemia, increased frequency of blood glucose monitoring is recommended.

5.4 Hypoglycemia Due to Medication Errors

Accidental mix-ups between insulin products have been reported. To avoid medication errors between HUMALOG Mix50/50 and other insulins, instruct patients to always check the insulin label before each injection.

5.5 Hypersensitivity Reactions

Severe, life-threatening, generalized allergy, including anaphylaxis, can occur with insulins, including HUMALOG Mix50/50. If hypersensitivity reactions occur, discontinue HUMALOG Mix50/50; treat per standard of care and monitor until symptoms and signs resolve. HUMALOG Mix50/50 is contraindicated in patients who have had hypersensitivity reactions to HUMALOG Mix50/50 or any of its excipients [see Contraindications (4)].

5.6 Hypokalemia

All insulins, including HUMALOG Mix50/50, cause a shift in potassium from the extracellular to intracellular space, possibly leading to hypokalemia. Untreated hypokalemia may cause respiratory paralysis, ventricular arrhythmia, and death. Monitor potassium levels in patients at risk for hypokalemia if indicated (e.g., patients using potassium-lowering medications, patients taking medications sensitive to serum potassium concentrations).

5.7 Fluid Retention and Heart Failure with Concomitant Use of PPAR-gamma Agonists

Thiazolidinediones (TZDs), which are peroxisome proliferator-activated receptor (PPAR)-gamma agonists, can cause dose-related fluid retention, particularly when used in combination with insulin. Fluid retention may lead to or exacerbate heart failure. Patients treated with insulin, including HUMALOG Mix50/50, and a PPAR-gamma agonist should be observed for signs and symptoms of heart failure. If heart failure develops, it should be managed according to current standards of care, and discontinuation or dose reduction of the PPAR-gamma agonist must be considered.

6 ADVERSE REACTIONS

The following adverse reactions are discussed elsewhere in the labeling:

- Hypoglycemia [see Warnings and Precautions (5.3)]
- Hypoglycemia Due to Medication Errors [see Warnings and Precautions (5.4)]
- Hypersensitivity Reactions [see Warnings and Precautions (5.5)]
- Hypokalemia [see Warnings and Precautions (5.6)]

Adverse Reactions from Clinical Studies or Postmarketing Reports

The following adverse reactions have been identified during post-marketing use of HUMALOG Mix50/50. Because some of these reactions are reported voluntarily from a population of uncertain size, it is not always possible to reliably estimate their frequency or establish a causal relationship to drug exposure.

Adverse reactions associated with insulin initiation and glucose control intensification

Intensification or rapid improvement in glucose control has been associated with a transitory, reversible ophthalmologic refraction disorder, worsening of diabetic retinopathy, and acute painful peripheral neuropathy. Over the long-term, improved glycemic control decreases the risk of diabetic retinopathy and neuropathy.

Hypersensitivity reactions

Severe, life-threatening, generalized allergy, including anaphylaxis.

Hypoglycemia

Hypoglycemia is the most commonly observed adverse reaction in HUMALOG Mix50/50.

Hypokalemia

HUMALOG Mix50/50 can cause a shift in potassium from the extracellular to intracellular space, possibly leading to hypokalemia.

Injection site reactions

HUMALOG Mix50/50 can cause local injection site reactions including redness, swelling, or itching at the site of injection. These reactions usually resolve in a few days to a few weeks, but in some occasions, may require discontinuation. Localized reactions and generalized myalgias have been reported with the use of meta-cresol, which is an excipient in HUMALOG Mix50/50.

Lipodystrophy

Administration of insulin subcutaneously, including HUMALOG Mix50/50, has resulted in lipoatrophy (depression in the skin) or lipohypertrophy (enlargement or thickening of tissue) [see Dosage and Administration (2.1)] in some patients.

Localized cutaneous amyloidosis

Localized cutaneous amyloidosis at the injection site has occurred. Hyperglycemia has been reported with repeated insulin injections into areas of localized cutaneous amyloidosis; hypoglycemia has been reported with a sudden change to an unaffected injection site.

Medication Errors

Medication errors in which other insulins have been accidentally substituted for HUMALOG Mix50/50 have been identified during postapproval use.

Peripheral Edema

Insulins, including HUMALOG Mix50/50, may cause sodium retention and edema, particularly if previously poor metabolic control is improved by intensified insulin therapy.

Weight gain

Weight gain can occur with insulins, including HUMALOG Mix50/50, and has been attributed to the anabolic effects of insulin and the decrease in glycosuria.

Immunogenicity

As with all therapeutic proteins, insulin administration may cause anti-insulin antibodies to form. The incidence of antibody formation with HUMALOG Mix50/50 is unknown.

7 DRUG INTERACTIONS

Table 1 describes the clinically significant drug interactions with HUMALOG Mix50/50.

Table 1: Clinically Significant Drug Interactions with HUMALOG Mix50/50
Drugs that May Increase the Risk of Hypoglycemia
Drugs: | Antidiabetic agents, ACE inhibitors, angiotensin II receptor blocking agents, disopyramide, fibrates, fluoxetine, monoamine oxidase inhibitors, pentoxifylline, pramlintide, salicylates, somatostatin analog (e.g., octreotide), and sulfonamide antibiotics.
Intervention: | Dose adjustment and increased frequency of glucose monitoring may be required when HUMALOG Mix50/50 is co-administered with these drugs.
Drugs that May Decrease the Blood Glucose Lowering Effect of HUMALOG Mix50/50
Drugs: | Atypical antipsychotics (e.g., olanzapine and clozapine), corticosteroids, danazol, diuretics, estrogens, glucagon, isoniazid, niacin, oral contraceptives, phenothiazines, progestogens (e.g., in oral contraceptives), protease inhibitors, somatropin, sympathomimetic agents (e.g., albuterol, epinephrine, terbutaline), and thyroid hormones.
Intervention: | Dose adjustment and increased frequency of glucose monitoring may be required when HUMALOG Mix50/50 is co-administered with these drugs.
Drugs that May Increase or Decrease the Blood Glucose Lowering Effect of HUMALOG Mix50/50
Drugs: | Alcohol, beta-blockers, clonidine, and lithium salts. Pentamidine may cause hypoglycemia, which may sometimes be followed by hyperglycemia.
Intervention: | Dose adjustment and increased frequency of glucose monitoring may be required when HUMALOG Mix50/50 is co-administered with these drugs.
Drugs that May Blunt Signs and Symptoms of Hypoglycemia
Drugs: | Beta-blockers, clonidine, guanethidine, and reserpine.
Intervention: | Increased frequency of glucose monitoring may be required when HUMALOG Mix50/50 is co-administered with these drugs.

8 USE IN SPECIFIC POPULATIONS

8.1 Pregnancy

Risk Summary

Published studies with insulin lispro used during pregnancy have not reported an association between insulin lispro and the induction of major birth defects, miscarriage, or adverse maternal or fetal outcomes (see Data). There are risks to the mother and fetus associated with poorly controlled diabetes in pregnancy (see Clinical Considerations).

Pregnant rats and rabbits were exposed to insulin lispro in animal reproduction studies during organogenesis. No adverse effects on embryo/fetal viability or morphology were observed in offspring of rats exposed to insulin lispro at a dose approximately 3 times the human subcutaneous dose of 1 unit insulin lispro/kg/day. No adverse effects on embryo/fetal development were observed in offspring of rabbits exposed to insulin lispro at doses up to approximately 0.2 times the human subcutaneous dose of 1 unit/kg/day (see Data).

The estimated background risk of major birth defects is 6-10% in women with pre-gestational diabetes with a HbA1c >7 and has been reported to be as high as 20-25% in women with a HbA1c >10. The estimated background risk of miscarriage for the indicated population is unknown. In the U.S. general population, the estimated background risk of major birth defects and miscarriage in clinically recognized pregnancies is 2-4% and 15-20%, respectively.

Clinical Considerations

Disease-associated maternal and/or embryo/fetal risk

Poorly controlled diabetes in pregnancy increases the maternal risk for diabetic ketoacidosis, pre-eclampsia, spontaneous abortions, preterm delivery, and delivery complications. Poorly controlled diabetes increases the fetal risk for major birth defects, still birth, and macrosomia related morbidity.

Data

Human Data

Published data from retrospective studies and meta-analyses do not report an association with insulin lispro and major birth defects, miscarriage, or adverse maternal or fetal outcomes when insulin lispro is used during pregnancy. However, these studies cannot definitely establish or exclude the absence of any risk because of methodological limitations including small sample size, selection bias, confounding by unmeasured factors, and some lacking comparator groups.

Animal Data

Animal reproduction studies have not been performed with HUMALOG Mix50/50. However, subcutaneous reproduction and teratology studies have been conducted with insulin lispro (a component of HUMALOG Mix50/50). In a combined fertility and embryo-fetal development study, female rats were given subcutaneous insulin lispro injections of 1, 5, and 20 units/kg/day (0.2, 0.8, and 3 times the human subcutaneous dose of 1 unit insulin lispro/kg/day, based on units/body surface area, respectively) from 2 weeks prior to cohabitation through Gestation Day 19. There were no adverse effects on female fertility, implantation, or fetal viability and morphology. However, fetal growth retardation was produced at the 20 units/kg/day-dose as indicated by decreased fetal weight and an increased incidence of fetal runts/litter.

In an embryo-fetal development study in pregnant rabbits, insulin lispro doses of 0.1, 0.25, and 0.75 unit/kg/day (0.03, 0.08, and 0.2 times the human subcutaneous dose of 1 unit insulin lispro/kg/day, based on units/body surface area, respectively) were injected subcutaneously on Gestation days 7 through 19. There were no adverse effects on fetal viability, weight, and morphology at any dose.

8.2 Lactation

Risk Summary

Available data from published literature suggests that exogenous human insulin products, including insulin lispro, are transferred into human milk. There are no adverse reactions reported in breastfed infants in the literature. There are no data on the effects of exogenous human insulin products, including insulin lispro, on milk production. The developmental and health benefits of breastfeeding should be considered along with the mother's clinical need for insulin, any potential adverse effects on the breastfed child from HUMALOG Mix50/50 or from the underlying maternal condition.

8.4 Pediatric Use

Safety and effectiveness of HUMALOG Mix50/50 in pediatric patients have not been established.

8.5 Geriatric Use

Clinical studies of Humalog Mix50/50 did not include sufficient numbers of patients aged 65 and over to determine whether they respond differently than younger patients. In elderly patients with diabetes, the initial dosing, dose increments, and maintenance dosage should be conservative to reduce the risk of hypoglycemia [see Warnings and Precautions (5.3)].

8.6 Renal Impairment

The effect of renal impairment on the pharmacokinetics of HUMALOG Mix50/50 has not been studied. Patients with renal impairment may be at increased risk of hypoglycemia and may require more frequent HUMALOG Mix50/50 dose adjustment and more frequent glucose monitoring [see Warnings and Precautions (5.3)].

8.7 Hepatic Impairment

The effect of hepatic impairment on the pharmacokinetics of HUMALOG Mix50/50 has not been studied. Patients with hepatic impairment may be at increased risk of hypoglycemia and may require more frequent HUMALOG Mix50/50 dose adjustment and more frequent glucose monitoring [see Warnings and Precautions (5.3)].

10 OVERDOSAGE

Excess insulin administration may cause hypoglycemia and hypokalemia. Mild episodes of hypoglycemia usually can be treated with oral glucose. Adjustments in drug dosage, meal patterns, or exercise may be needed. More severe episodes with coma, seizure, or neurologic impairment may be treated with a glucagon product for emergency use or concentrated intravenous glucose. Sustained carbohydrate intake and observation may be necessary because hypoglycemia may recur after apparent clinical recovery. Hypokalemia must be corrected appropriately [see Warnings and Precautions (5.3, 5.6)].

11 DESCRIPTION

Insulin lispro is a rapid-acting insulin analog produced by recombinant DNA technology utilizing a non-pathogenic laboratory strain of Escherichia coli. Insulin lispro differs from human insulin in that the amino acid proline at position B28 is replaced by lysine and the lysine in position B29 is replaced by proline. Chemically, it is Lys(B28), Pro(B29) human insulin analog and has the empirical formula C257H383N65O77S6 and a molecular weight of 5.808 kDa, both identical to that of human insulin.

Humalog Mix50/50 (insulin lispro protamine and insulin lispro) injectable suspension is a mixture of 50% insulin lispro protamine, an intermediate-acting human insulin analog, and 50% insulin lispro, a rapid-acting human insulin analog. Insulin lispro protamine suspension is a suspension of crystals produced from combining insulin lispro and protamine sulfate under appropriate conditions for crystal formation.

Insulin lispro has the following primary structure:

HUMALOG Mix50/50 (insulin lispro protamine and insulin lispro) injectable suspension is a sterile, white and cloudy suspension for subcutaneous use.

Each mL of HUMALOG Mix50/50 contains 100 units of insulin lispro; dibasic sodium phosphate (2.0 mg), glycerin (16 mg), metacresol (2.20 mg), phenol (0.89 mg), protamine sulfate (0.19 mg), zinc oxide content adjusted to provide zinc ion (0.0305 mg), and Water for Injection, USP. The pH is 7.0 to 7.8. Sodium hydroxide and/or hydrochloric acid is added during manufacture to adjust the pH.

12 CLINICAL PHARMACOLOGY

12.1 Mechanism of Action

The primary activity of insulin including HUMALOG Mix50/50 is the regulation of glucose metabolism. Insulins lower blood glucose by stimulating peripheral glucose uptake by skeletal muscle and fat, and by inhibiting hepatic glucose production. Insulins inhibit lipolysis and proteolysis, and enhance protein synthesis.

12.2 Pharmacodynamics

In a glucose clamp study performed in 30 healthy subjects, the onset of action and glucose-lowering activity of HUMALOG, HUMALOG Mix50/50, HUMALOG® Mix75/25™, and insulin lispro protamine suspension (ILPS) were compared (see Figure 1). Graphs of mean glucose infusion rate versus time showed a distinct insulin activity profile for each formulation. The rapid onset of glucose-lowering activity characteristic of HUMALOG was maintained in HUMALOG Mix50/50. The median maximum pharmacologic effect of HUMALOG Mix50/50 after administration of a 0.3 unit/kg dose to healthy subjects occurred at 2 hours (range: 1-5 hours); glucose lowering activity was detectable for a median of 22 hours (range: 11 to 22 hours), which was the end of the clamp.

Figure 1 should be considered only as a representative example since the time course of action of insulin and insulin analogs, may vary in different individuals or within the same individual.

Figure 1: Mean Insulin Activity Versus Time Profiles After Injection of 0.3 units/kg of HUMALOG, HUMALOG Mix50/50, HUMALOG Mix75/25, or Insulin Lispro Protamine Suspension (ILPS) in 30 Healthy Subjects.

12.3 Pharmacokinetics

Absorption — HUMALOG Mix50/50 has two phases of absorption. The early phase represents insulin lispro and its distinct characteristics of rapid onset. The late phase represents the prolonged absorption of insulin lispro protamine suspension.

In 30 healthy subjects given subcutaneous doses (0.3 unit/kg) of HUMALOG Mix50/50, the median peak serum concentration occurred at 60 minutes (range: 45 minutes to 13.5 hours) after dosing. In patients with type 1 diabetes, the median peak serum concentration occurred at 60 minutes (range: 45 minutes to 2 hours) after dosing.

Metabolism — Human metabolism studies of HUMALOG Mix50/50 have not been conducted. However, studies in animals indicate that the metabolism of HUMALOG, the rapid-acting component of HUMALOG Mix50/50, is identical to that of regular human insulin.

Elimination — Because of the absorption-rate limited kinetics of insulin mixtures, a true half-life cannot be accurately estimated from the terminal slope of the concentration versus time curve.

Specific Populations

The effects of age, race, obesity, pregnancy, smoking, or renal or hepatic impairment on the pharmacokinetics of HUMALOG Mix50/50 have not been studied.

Gender — Pharmacokinetic and pharmacodynamic comparisons between men and women administered HUMALOG Mix50/50 showed no gender differences.

13 NONCLINICAL TOXICOLOGY

13.1 Carcinogenesis, Mutagenesis, Impairment of Fertility

Standard 2-year carcinogenicity studies in animals have not been performed with HUMALOG Mix50/50. In Fischer 344 rats, a 12-month repeat-dose toxicity study was conducted with insulin lispro (a component of HUMALOG Mix50/50) at subcutaneous doses of 20 and 200 units/kg/day (approximately 3 and 32 times the human subcutaneous dose of 1 unit insulin lispro/kg/day, based on units/body surface area). Insulin lispro did not produce important target organ toxicity including mammary tumors at any dose.

Insulin lispro was not mutagenic in the following genetic toxicity assays: bacterial mutation, unscheduled DNA synthesis, mouse lymphoma, chromosomal aberration and micronucleus assays.

Male fertility was not compromised when male rats given subcutaneous insulin lispro injections of 5 and 20 units/kg/day (0.8 and 3 times the human subcutaneous dose of 1 unit insulin lispro/kg/day, based on units/body surface area) for 6 months were mated with untreated female rats. In a combined fertility, perinatal, and postnatal study in male and female rats given 1, 5, and 20 units/kg/day subcutaneously (0.2, 0.8, and 3 times the human subcutaneous dose of 1 unit insulin lispro/kg/day, based on units/body surface area), mating and fertility were not adversely affected in either gender at any dose.

16 HOW SUPPLIED/STORAGE AND HANDLING

16.1 How Supplied

HUMALOG Mix50/50 (insulin lispro protamine and insulin lispro) injectable suspension, is a white and cloudy suspension of 100 units/mL (U-100) of 50% insulin lispro protamine and 50% insulin lispro available as:

One 10 mL multiple-dose vial | NDC 0002-7512-01
Five 3 mL single-patient-use KwikPen prefilled pens | NDC 0002-8798-59

HUMALOG Mix50/50 KwikPen must never be shared between patients, even if the needle is changed. Patients using HUMALOG Mix50/50 vials must never share needles or syringes with another person. Always use a new disposable syringe or needle for each injection to prevent contamination.

The HUMALOG Mix50/50 KwikPen dials in 1 unit increments.

16.2 Storage and Handling

Dispense in the original sealed carton with the enclosed Instructions for Use.

Protect from direct heat and light. Do not freeze and do not use if it has been frozen. See storage table below:

 | Not In-Use (Unopened) Refrigerated (36° to 46°F [2° to 8°C]) | Not In-Use (Unopened) Room Temperature (up to 86°F [30°C]) | In-Use (Opened) (see temperature below)
10 mL multiple-dose viala | Until expiration date | 28 days | 28 days Refrigerated or room temperature
3 mL single-patient-use KwikPenb prefilled pen | Until expiration date | 10 days | 10 days Room temperature only (Do not refrigerate)
a When stored at room temperature, HUMALOG Mix50/50 vial can only be used for a total of 28 days including both not in use (unopened) and in-use (opened) storage time.
b When stored at room temperature, HUMALOG Mix50/50 KwikPen can only be used for a total of 10 days including both not in-use (unopened) and in-use (opened) storage time.

17 PATIENT COUNSELING INFORMATION

Advise the patient to read the FDA-approved patient labeling (Patient Information and Instructions for Use).

Never Share a HUMALOG Mix50/50 KwikPen or Syringe Between Patients

Advise patients using Humalog Mix50/50 vials or Humalog Mix50/50 KwikPen not to share needles, syringes, or KwikPen with another person. Sharing poses a risk for transmission of blood-borne pathogens [see Warnings and Precautions (5.1)].

Hyperglycemia or Hypoglycemia

Inform patients that hypoglycemia is the most common adverse reaction with insulin. Instruct patients on self-management procedures including glucose monitoring, proper injection technique, and management of hypoglycemia and hyperglycemia, especially at initiation of HUMALOG Mix50/50 therapy. Instruct patients on handling of special situations such as intercurrent conditions (illness, stress, or emotional disturbances), an inadequate or skipped insulin dose, inadvertent administration of an increased insulin dose, inadequate food intake, and skipped meals. Instruct patients on the management of hypoglycemia [see Warnings and Precautions (5.3)].

Inform patients that their ability to concentrate and react may be impaired as a result of hypoglycemia. Advise patients who have frequent hypoglycemia or reduced or absent warning signs of hypoglycemia to use caution when driving or operating machinery.

Advise patients that changes in insulin regimen can predispose to hyperglycemia or hypoglycemia and that changes in insulin regimen should be made under close medical supervision [see Warnings and Precautions (5.2)].

Hypoglycemia due to Medication Errors

Instruct patients to always check the insulin label before each injection to avoid mix-ups between insulin products [see Warnings and Precautions (5.4)].

Hypersensitivity Reactions

Advise patients that hypersensitivity reactions have occurred with HUMALOG Mix50/50. Inform patients on the symptoms of hypersensitivity reactions and to seek medical attention if they occur [see Warnings and Precautions (5.5)].

Manufactured by:
Eli Lilly and Company
Indianapolis, IN 46285, USA
US License Number 1891

Copyright © 1999, 2023, Eli Lilly and Company. All rights reserved.

LOG5050-0007-USPI-20230721

PATIENT PACKAGE INFORMATION

PATIENT INFORMATION
HUMALOG® (HU-ma-log) Mix50/50™
(insulin lispro protamine and insulin lispro)
injectable suspension, for subcutaneous use

Do not share your HUMALOG Mix50/50 KwikPen, needles or syringes with other people, even if the needle has been changed. You may give other people a serious infection or get a serious infection from them.

What is HUMALOG Mix50/50?

- HUMALOG Mix50/50 is a man-made insulin that is used to control high blood sugar in adults with diabetes mellitus.
- It is not known if HUMALOG Mix50/50 is safe and effective in children under 18 years of age.

Who should not take HUMALOG Mix50/50?
Do not take HUMALOG Mix50/50 if you:

- are having an episode of low blood sugar (hypoglycemia).
- have an allergy to HUMALOG Mix50/50 or any of the ingredients in HUMALOG Mix50/50. See the end of this Patient Information leaflet for a complete list of ingredients in Humalog Mix50/50.

What should I tell my healthcare provider before taking Humalog Mix50/50?
Before taking HUMALOG Mix50/50, tell your healthcare provider about all of your medical conditions, including if you:

- have liver or kidney problems.
- take any other medicines, especially ones called TZDs (thiazolidinediones).
- have heart failure or other heart problems. If you have heart failure, it may get worse while you take TZDs with HUMALOG Mix50/50.
- are pregnant or plan to become pregnant. Talk with your healthcare provider about the best way to control your blood sugar if you plan to become pregnant or while you are pregnant.
- are breastfeeding or plan to breastfeed. Talk with your healthcare provider about the best way to feed your baby while taking HUMALOG Mix50/50.

Tell your healthcare provider about all the medicines you take, including prescription and over-the-counter medicines, vitamins and herbal supplements.
Before you start taking HUMALOG Mix50/50, talk to your healthcare provider about low blood sugar and how to manage it.

How should I take HUMALOG Mix50/50?

- Read the Instructions for Use that comes with your HUMALOG Mix50/50.
- Take HUMALOG Mix50/50 exactly as your healthcare provider tells you to. Your healthcare provider should tell you how much HUMALOG Mix50/50 to take and when to take it.
- HUMALOG Mix50/50 starts acting fast. Inject HUMALOG Mix50/50 within 15 minutes before you eat a meal.
- Know the type, strength, and amount of insulin you take. Do not change the type or amount of insulin you take unless your healthcare provider tells you to. The amount of insulin and the best time for you to take your insulin may need to change if you take different types of insulin.
- Check your insulin label each time you give your injection to make sure you are taking the correct insulin.
- Inject Humalog Mix50/50 under the skin (subcutaneously) of your stomach area (abdomen), buttocks, upper legs or upper arms. Do not inject HUMALOG Mix50/50 into your vein (intravenously) or use in an insulin infusion pump.
- Change (rotate) your injection sites within the area you choose with each dose to reduce your risk of getting lipodystrophy (pits in skin or thickened skin) and localized cutaneous amyloidosis (skin with lumps) at the injection sites.
  - Do not use the exact same spot for each injection.
  - Do not inject where the skin has pits, is thickened, or has lumps.
  - Do not inject where the skin is tender, bruised, scaly or hard, or into scars or damaged skin.
- Do not mix Humalog Mix50/50 with other insulins or liquids.
- Check your blood sugar levels. Ask your healthcare provider what your blood sugars should be and when you should check your blood sugar levels.

Keep HUMALOG Mix50/50 and all medicines out of reach of children.

Your dose of HUMALOG Mix50/50 may need to change because of a:

- change in physical activity or exercise, weight gain or loss, increased stress, illness, change in diet, or because of other medicines you take.

What should I avoid while taking HUMALOG Mix50/50?
While taking HUMALOG Mix50/50 do not:

- drive or operate heavy machinery until you know how HUMALOG Mix50/50 affects you.
- drink alcohol or take prescription or over-the-counter medicines that contain alcohol.

What are the possible side effects of HUMALOG Mix50/50?
HUMALOG Mix50/50 may cause serious side effects that can lead to death, including:

- low blood sugar (hypoglycemia). Signs and symptoms of low blood sugar may include:

- dizziness or light-headedness
- sweating
- confusion
- headache
- blurred vision

- slurred speech
- shakiness
- fast heartbeat
- anxiety, irritability or mood changes
- hunger

Your healthcare provider may prescribe a glucagon product for emergency use so that someone else can give you glucagon if your blood sugar becomes too low (severe hypoglycemia) and you are unable to take sugar by mouth.

- severe allergic reaction (whole body reaction). Get medical help right away, if you have any of these signs or symptoms of a severe allergic reaction:

- a rash over your whole body
- trouble breathing

- fast heartbeat
- sweating

- low potassium in your blood (hypokalemia).
- heart failure. Taking certain diabetes pills called thiazolidinediones or “TZDs” with HUMALOG Mix50/50 may cause heart failure in some people. This can happen even if you have never had heart failure or heart problems before. If you already have heart failure it may get worse while you take TZDs with HUMALOG Mix50/50. Your healthcare provider should monitor you closely while you are taking TZDs with HUMALOG Mix50/50. Tell your healthcare provider if you have any new or worse symptoms of heart failure including:

- shortness of breath
- swelling of your ankles or feet

- sudden weight gain

Treatment with TZDs and HUMALOG Mix50/50 may need to be adjusted or stopped by your healthcare provider if you have new or worse heart failure.
Get emergency medical help if you have:

- fast heartbeat
- sweating
- extreme drowsiness
- dizziness

- confusion
- shortness of breath
- trouble breathing
- swelling of your face, tongue, or throat

The most common side effects of HUMALOG Mix50/50 include:

- low blood sugar (hypoglycemia)
- reactions at your injection site
- skin thickening or pits at the injection site (lipodystrophy)

- weight gain
- swelling in your hands or feet
- itching
- rash

These are not all the possible side effects of HUMALOG Mix50/50. Call your doctor for medical advice about side effects. You may report side effects to FDA at 1-800-FDA-1088.

General information about the safe and effective use of HUMALOG Mix50/50.
Medicines are sometimes prescribed for purposes other than those listed in a Patient Information leaflet. Do not take HUMALOG Mix50/50 for a condition for which it was not prescribed. Do not give HUMALOG Mix50/50 to other people, even if they have the same symptoms that you have. It may harm them.
This Patient Information leaflet summarizes the most important information about HUMALOG Mix50/50. If you would like more information, talk with your healthcare provider. You can ask your pharmacist or healthcare provider for information about HUMALOG Mix50/50 that is written for health professionals.

What are the ingredients in HUMALOG Mix50/50?
Active ingredients: insulin lispro
Inactive ingredients: dibasic sodium phosphate, glycerin, hydrochloric acid, metacresol, phenol, protamine sulfate, sodium hydroxide, zinc oxide (zinc ion), and Water for Injection, USP.

Humalog®, Humalog® Mix50/50™ and Humalog® Mix50/50™ KwikPen® are trademarks of Eli Lilly and Company.
Manufactured by: Eli Lilly and Company, Indianapolis, IN 46285, USA, US License Number 1891
Copyright © 1999, 2023, Eli Lilly and Company. All rights reserved.
For more information, go to www.humalog.com or call 1-800-545-5979.

This Patient Information has been approved by the U.S. Food and Drug Administration.

Revised: 07/2023

LOG5050-0004-PPI-20230721

VIAL INSTRUCTIONS FOR USE

INSTRUCTIONS FOR USE

HUMALOG® (HU-ma-log) Mix50/50™

(insulin lispro protamine and insulin lispro)

injectable suspension, for subcutaneous use

10 mL multiple-dose vial (100 units per mL)

Read this Instructions for Use before you start taking HUMALOG Mix50/50 and each time you get a new vial. There may be new information. This information does not take the place of talking to your healthcare provider about your medical condition or your treatment.

Do not share your needles or syringes with other people, even if the needle has been changed. You may give other people a serious infection or get a serious infection from them.

Supplies needed to give your injection

- a multiple-dose HUMALOG Mix50/50 vial
- a U-100 insulin syringe and needle
- 2 alcohol swabs
- gauze
- 1 sharps container for throwing away used needles and syringes. See “Disposing of used needles and syringes” at the end of these instructions.

Vial

Syringe

Preparing your HUMALOG Mix50/50 dose

- Wash your hands with soap and water.
- Check the HUMALOG Mix50/50 label to make sure you are taking the right type of insulin. This is especially important if you use more than 1 type of insulin.
- HUMALOG Mix50/50 is easier to mix when it is at room temperature.
- After mixing HUMALOG Mix50/50, inject your dose right away. If you wait to inject your dose, the insulin will need to be mixed again.
- Always use a new syringe and needle for each injection to help prevent infections and blocked needles. Do not reuse or share your syringes or needles with other people. You may give other people a serious infection or get a serious infection from them.

Step 1:
Gently roll the vial between the palms of your hands at least 10 times.

Step 2:
Gently move the vial up and down (invert) at least 10 times.
Mixing is important to make sure you get the right dose. Humalog Mix50/50 should look white and cloudy after mixing. Do not use it if it looks clear or contains any lumps or particles.

Step 3:
If you are using a new vial, pull off the plastic Protective Cap, but do not remove the Rubber Stopper.

Step 4:
Wipe the Rubber Stopper with an alcohol swab.

Step 5:
Remove the Needle Shield from the syringe by pulling the Needle Shield straight off. Hold the syringe with the needle pointing up. Pull down on the Plunger until the Plunger Tip reaches the line for the number of units for your prescribed dose.

(Example Dose: 20 units shown)

Step 6:
Push the needle through the Rubber Stopper of the vial.

Step 7:
Push the Plunger all the way in. This puts air into the vial.

Step 8:
Turn the vial and syringe upside down and slowly pull the Plunger down until the Plunger Tip is a few units past the line for your prescribed dose.

(Example Dose: 20 units
Plunger Tip is shown at 24 units)

If there are air bubbles, tap the syringe gently a few times to let any air bubbles rise to the top.

Step 9:
Slowly push the Plunger up until the Plunger Tip reaches the line for your prescribed dose.
Check the syringe to make sure that you have the right dose.

(Example Dose: 20 units shown)

Step 10:
Pull the syringe out of the Rubber Stopper of the vial.

Giving your HUMALOG Mix50/50 injection

- Inject your insulin exactly as your healthcare provider has shown you. Your healthcare provider should tell you if you should pinch the skin before injecting.
- Change (rotate) your injection sites within the area you choose for each dose to reduce your risk of getting lipodystrophy (pits in skin or thickened skin) and localized cutaneous amyloidosis (skin with lumps) at the injection sites.
- Do not inject where the skin has pits, is thickened, or has lumps.
- Do not inject where the skin is tender, bruised, scaly or hard, or into scars or damaged skin.

Step 11:
Choose your injection site.
HUMALOG Mix50/50 is injected under the skin (subcutaneously) of your stomach area (abdomen), buttocks, upper legs or upper arms.
Wipe the skin with an alcohol swab. Let the injection site dry before you inject your dose.

Step 12:
Insert the needle into your skin.

Step 13:
Push down on the Plunger to inject your dose.
The needle should stay in your skin for at least 5 seconds to make sure you have injected all of your insulin dose.

Step 14:
Pull the needle out of your skin.

- If you see blood after you take the needle out of your skin, press the injection site with a piece of gauze or an alcohol swab. Do not rub the area.
- Do not recap the needle. Recapping the needle can lead to a needle stick injury.

Disposing of used needles and syringes

- Put your used needles and syringes in a FDA-cleared sharps disposal container right away after use. Do not throw away (dispose of) loose needles and syringes in your household trash.
- If you do not have a FDA-cleared sharps disposal container, you may use a household container that is:
  - made of a heavy-duty plastic,
  - can be closed with a tight-fitting, puncture-resistant lid, without sharps being able to come out,
  - upright and stable during use,
  - leak-resistant, and
  - properly labeled to warn of hazardous waste inside the container.
- When your sharps disposal container is almost full, you will need to follow your community guidelines for the right way to dispose of your sharps disposal container. There may be state or local laws about how you should throw away used needles and syringes. For more information about safe sharps disposal, and for specific information about sharps disposal in the state that you live in, go to the FDA's website at:
  http://www.fda.gov/safesharpsdisposal.
- Do not dispose of your used sharps disposal container in your household trash unless your community guidelines permit this. Do not recycle your used sharps disposal container.

How should I store HUMALOG Mix50/50?

All unopened vials:

- Store all unopened vials in the refrigerator at 36°F to 46°F (2°C to 8°C).
- Do not freeze. Do not use if HUMALOG Mix50/50 has been frozen.
- Keep away from heat and out of direct light.
- Unopened vials can be used until the expiration date on the carton and label, if they have been stored in the refrigerator.
- Unopened vials should be thrown away after 28 days, if they are stored at room temperature.

After vials have been opened:

- Store opened vials in the refrigerator or at room temperature up to 86°F (30°C) for up to 28 days.
- Keep vials away from heat and out of direct light.
- Throw away all opened vials after 28 days of use, even if there is insulin left in the vial.

Keep HUMALOG Mix50/50 vials, syringes, needles, and all medicines out of the reach of children.

If you have any questions or problems with your HUMALOG, contact Lilly at 1-800-Lilly-Rx (1-800-545-5979) or call your healthcare provider for help. For more information on HUMALOG and insulin, go to www.humalog.com.

Manufactured by:
Eli Lilly and Company
Indianapolis, IN 46285, USA
US License Number 1891

This Instructions for Use has been approved by the U.S. Food and Drug Administration.

Revised: 07/2023

Scan this code to launch the humalog.com website

Humalog® and Humalog® Mix50/50™ are registered trademarks of Eli Lilly and Company.

Copyright © 1999, 2023, Eli Lilly and Company. All rights reserved.

LOG5050VL-0003-IFU-20230721

KWIKPEN (U-100) INSTUCTIONS FOR USE

INSTRUCTIONS FOR USE

HUMALOG® (HU-ma-log) Mix50/50™ KwikPen®

(insulin lispro protamine and insulin lispro)

injectable suspension, for subcutaneous use

3 mL single-patient-use pen (100 units per mL)

Read this Instructions for Use before you start taking HUMALOG Mix50/50 and each time you get another KwikPen. There may be new information. This information does not take the place of talking to your healthcare provider about your medical condition or your treatment.

Do not share your HUMALOG Mix50/50 KwikPen with other people, even if the needle has been changed. You may give other people a serious infection or get a serious infection from them.

HUMALOG Mix50/50 KwikPen (“Pen”) is a disposable single-patient-use prefilled pen containing 300 units of HUMALOG Mix50/50.

- You can give yourself more than 1 dose from the Pen.
- By turning the Dose Knob, you can dial doses from 1 to 60 units in 1 unit increments.
- If your dose is more than 60 units, you will need to give yourself more than 1 injection.
- The Plunger only moves a little with each injection, and you may not notice that it moves. The Plunger will only reach the end of the cartridge when you have used all 300 units in the Pen.

People who are blind or have vision problems should not use this Pen without help from a person trained to use the Pen.

How to recognize your HUMALOG Mix50/50 KwikPen

- Pen color: Dark blue
- Dose Knob: Dark blue
- Labels: White label with red stripe

Supplies you will need to give your injection

- HUMALOG Mix50/50 KwikPen
- KwikPen compatible Needle (Becton, Dickinson and Company Pen Needles recommended)
- Alcohol swab
- Gauze

Preparing your Pen

- Wash your hands with soap and water.
- Check your Pen to make sure you are taking the right type of insulin. This is especially important if you use more than 1 type of insulin.
- Always use a new needle for each injection to help prevent infections and blocked needles. Do not reuse or share your needles with other people. You may give other people a serious infection or get a serious infection from them.

Step 1:

- Pull the Pen Cap straight off.
  - Do not remove the Pen Label.
- Wipe the Rubber Seal with an alcohol swab.
  - Do not attach the Needle before mixing.

Step 2:

- Gently roll the Pen between your hands at least 10 times.

Step 3:

- Move the Pen up and down (invert) at least 10 times.
  Mixing by rolling and inverting the Pen is important to make sure you get the right dose.
  After mixing HUMALOG Mix50/50, inject your dose right away. If you wait to inject your dose, the insulin will need to be mixed again.

Step 4:

- Check the liquid in the Pen. HUMALOG Mix50/50 should look white and cloudy after mixing. Do not use if it looks clear or has any lumps or particles in it.

Step 5:

- Select a new Needle.
- Pull off the Paper Tab from the Outer Needle Shield.

Step 6:

- Push the capped Needle straight onto the Pen and twist the Needle on until it is tight.

Step 7:

- Pull off the Outer Needle Shield. Do not throw it away.
- Pull off the Inner Needle Shield and throw it away.

Priming your Pen

Prime your Pen before each injection.

- Priming your Pen means removing the air from the Needle and Cartridge that may collect during normal use and ensures that the Pen is working correctly.
- If you do not prime before each injection, you may get too much or too little insulin.

Step 8:

- To prime your Pen, turn the Dose Knob to select 2 units.

Step 9:

- Hold your Pen with the Needle pointing up. Tap the Cartridge Holder gently to collect air bubbles at the top.

Step 10:

- Continue holding your Pen with Needle pointing up. Push the Dose Knob in until it stops, and “0” is seen in the Dose Window. Hold the Dose Knob in and count to 5 slowly.
- You should see insulin at the tip of the Needle.
  - If you do not see insulin, repeat priming steps 8 to 10, no more than 4 times.
  - If you still do not see insulin, change the Needle and repeat priming steps 8 to 10.

Small air bubbles are normal and will not affect your dose.

Selecting your dose

- You can give from 1 to 60 units in a single injection.
- If your dose is more than 60 units, you will need to give more than one injection.
  - If you need help with dividing up your dose the right way, ask your healthcare provider.
  - Use a new Needle for each injection and repeat the priming steps.

Step 11:

- Turn the Dose Knob to select the number of units you need to inject. The Dose Indicator should line up with your dose.
  - The Pen dials 1 unit at a time.
  - The Dose Knob clicks as you turn it.
  - Do not dial your dose by counting the clicks. You may dial the wrong dose. This may lead to you getting too much insulin or not enough insulin.
  - The dose can be corrected by turning the Dose Knob in either direction until the correct dose lines up with the Dose Indicator.
  - The even numbers (for example, 12) are printed on the dial.
  - The odd numbers, (for example, 25) after the number 1, are shown as full lines.
- Always check the number in the Dose Window to make sure you have dialed the correct dose.

(Example: 12 units shown in the Dose Window)
(Example: 25 units shown in the Dose Window)

- The Pen will not let you dial more than the number of units left in the Pen.
- If you need to inject more than the number of units left in the Pen, you may either:
  - inject the amount left in your Pen and then use a new Pen to give the rest of your dose, or
  - get a new Pen and inject the full dose.
- It is normal to see a small amount of insulin left in the Pen that you can not inject.

Giving your injection

- Inject your insulin as your healthcare provider has shown you.
- Change (rotate) your injection sites within the area you choose for each dose to reduce your risk of getting lipodystrophy (pits in skin or thickened skin) and localized cutaneous amyloidosis (skin with lumps) at the injection sites.
- Do not inject where the skin has pits, is thickened, or has lumps.
- Do not inject where the skin is tender, bruised, scaly or hard, or into scars or damaged skin.
- Do not try to change your dose while injecting.

Step 12:

- Choose your injection site.
  HUMALOG Mix50/50 is injected under the skin (subcutaneously) of your stomach area, buttocks, upper legs or upper arms.
- Wipe your skin with an alcohol swab, and let your skin dry before you inject your dose.

Step 13:

- Insert the Needle into your skin.
- Push the Dose Knob all the way in.
- Continue to hold the Dose Knob in and slowly count to 5 before removing the Needle.
  Do not try to inject your insulin by turning the Dose Knob. You will not receive your insulin by turning the Dose Knob.

Step 14:

- Pull the Needle out of your skin.
  A drop of insulin at the Needle tip is normal. It will not affect your dose.
- Check the number in the Dose Window.
  - If you see “0” in the Dose Window, you have received the full amount you dialed.
  - If you do not see “0” in the Dose Window, do not redial. Insert the Needle into your skin and finish your injection.
  - If you still do not think you received the full amount you dialed for your injection, do not start over or repeat the injection. Monitor your blood glucose as instructed by your healthcare provider.
  - If you normally need to give 2 injections for your full dose, be sure to give your second injection.

The Plunger only moves a little with each injection, and you may not notice that it moves.
If you see blood after you take the Needle out of your skin, press the injection site lightly with a piece of gauze or an alcohol swab. Do not rub the area.

After your injection

Step 15:

- Carefully replace the Outer Needle Shield.

Step 16:

- Unscrew the capped Needle and throw it away (see Disposing of Pens and Needles section).
- Do not store the Pen with the Needle attached to prevent leaking, blocking the Needle, and air from entering the Pen.

Step 17:

- Replace the Pen Cap by lining up the Cap Clip with the Dose Indicator and pushing straight on.

Disposing of Pens and Needles

- The used Pen may be discarded in your household trash after you have removed the needle.
- Put your used needles in a FDA-cleared sharps disposal container right away after use. Do not throw away (dispose of) loose needles in your household trash.
- If you do not have a FDA-cleared sharps disposal container, you may use a household container that is:
  - made of a heavy-duty plastic,
  - can be closed with a tight-fitting, puncture-resistant lid, without sharps being able to come out,
  - upright and stable during use,
  - leak-resistant, and
  - properly labeled to warn of hazardous waste inside the container.
- When your sharps disposal container is almost full, you will need to follow your community guidelines for the right way to dispose of your sharps disposal container. There may be state or local laws about how you should throw away used needles and syringes. For more information about safe sharps disposal, and for specific information about sharps disposal in the state that you live in, go to the FDA's website at: http://www.fda.gov/safesharpsdisposal
- Do not dispose of your used sharps disposal container in your household trash unless your community guidelines permit this. Do not recycle your used sharps disposal container.

Storing your Pen

Unused Pens

- Store unused Pens in the refrigerator at 36°F to 46°F (2°C to 8°C).
- Do not freeze your insulin. Do not use if HUMALOG Mix50/50 has been frozen.
- Unused Pens may be used until the expiration date printed on the Label, if the Pen has been kept in the refrigerator.
- Unused Pens stored at room temperature, up to 86°F (30°C), should be thrown away after 10 days.

In-use Pen

- Store the Pen you are currently using at room temperature [up to 86°F (30°C)]. Keep away from heat and light.
- Throw away the HUMALOG Mix50/50 Pen you are using after 10 days, even if it still has insulin left in it.

General information about the safe and effective use of your Pen

- Keep your Pen and needles out of the reach of children.
- Do not use your Pen if any part looks broken or damaged.
- Always carry an extra Pen in case yours is lost or damaged.

Troubleshooting

- If you can not remove the Pen Cap, gently twist the cap back and forth, and then pull the cap straight off.
- If the Dose Knob is hard to push:
  - Pushing the Dose Knob more slowly will make it easier to inject.
  - Your Needle may be blocked. Put on a new Needle and prime the Pen.
  - You may have dust, food, or liquid inside the Pen. Throw the Pen away and get a new Pen.

If you have any questions or problems with your HUMALOG Mix50/50 KwikPen, contact Lilly at 1-800-LillyRx (1-800-545-5979) or call your healthcare provider for help. For more information on HUMALOG Mix50/50 KwikPen and insulin, go to www.humalog.com.

Manufactured by:
Eli Lilly and Company
Indianapolis, IN 46285, USA
US License Number 1891

This Instructions for Use has been approved by the U.S. Food and Drug Administration.

Revised: 07/2023

Scan this code to launch (www.humalog.com)

HUMALOG® Mix50/50™ and HUMALOG® Mix50/50™ KwikPen® are trademarks of Eli Lilly and Company.

Copyright © 2007, 2023, Eli Lilly and Company. All rights reserved.

HUMALOG Mix50/50 KwikPen meets the current dose accuracy and functional requirements of ISO 11608-1.

LOG5050KP-0006-IFU-20230721

PACKAGE LABEL

PACKAGE CARTON – HUMALOG Mix50/50 10 mL vial 1ct

NDC 0002-7512-01

Humalog® Mix50/50™

(insulin lispro protamine and insulin lispro) injectable suspension

100 units per mL (U-100)

For subcutaneous use only

10 mL multiple-dose vial

Use only with a U-100 syringe

Rx only

www.humalog.com

Lilly

PACKAGE CARTON – HUMALOG Mix50/50 KwikPen 5ct

NDC 0002-8798-59

Humalog® Mix50/50™

KwikPen®

(insulin lispro protamine and insulin lispro)
injectable suspension

For Single Patient Use Only

Dispense in this sealed carton.

Needles not included

100 units per mL (U-100)

This device is recommended for use with Becton, Dickinson and Company's insulin pen needles

For subcutaneous use only.

prefilled insulin delivery device

Rx only

5 x 3 mL Prefilled Pens

Read Insulin Delivery Device Instructions for Use